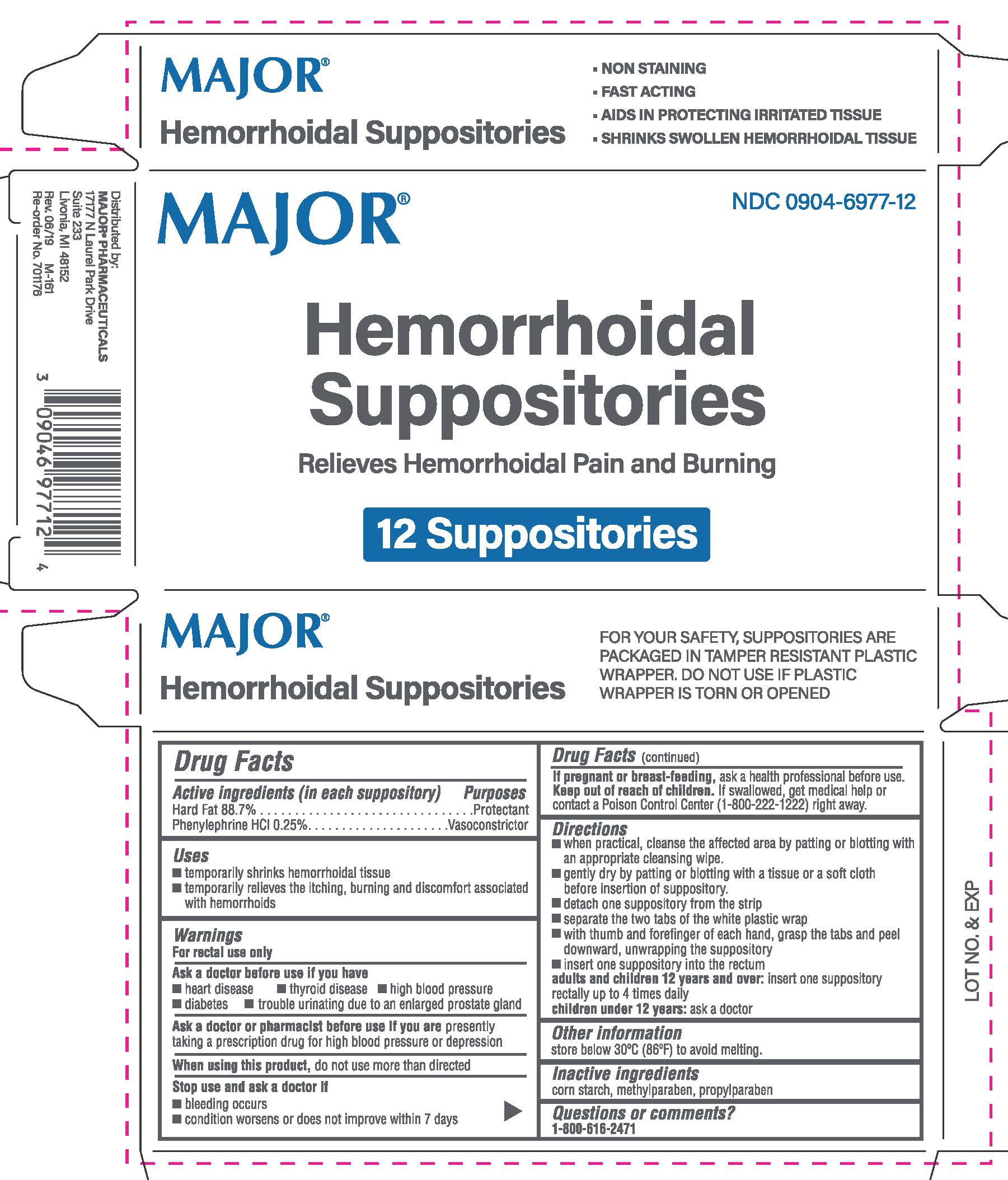 DRUG LABEL: Hemorrhoidal
NDC: 0904-6977 | Form: SUPPOSITORY
Manufacturer: Major Pharmaceuticals
Category: otc | Type: HUMAN OTC DRUG LABEL
Date: 20250801

ACTIVE INGREDIENTS: HARD FAT 1.77 g/1 1; PHENYLEPHRINE HYDROCHLORIDE 5 mg/1 1
INACTIVE INGREDIENTS: STARCH, CORN; METHYLPARABEN; PROPYLPARABEN

Major Hemorrhoidal Suppositories

Active Ingredients (in each suppository)

Hard Fat 88.44%

Phenylephrine hydrochloride 0.25%

Purpose

Protectant

Vasoconstrictor

Uses

- temporarily shrinks hemorrhoidal tissue
- gives temporary relief to the itching, burning and discomfort associated with hemorrhoids

Warnings

For rectal use only

Ask a doctor before use if you have

- heart disease
- thyroid disease
- high blood pressure
- diabetes
- trouble urinating due to an enlargedprostate gland

Ask a doctor or pharmacist before use if you are

presently taking a prescription drug for high blood pressure or depression

When using this product,

do not use more than directed

Stop use and ask a doctor if

- bleeding occurs
- condition worsens or does not improve within 7 days

If pregnant or breast-feeding,

ask a health professional before use.

Keep out of reach of children.

If swallowed, get medical help or contact a Poison Control Center (1-800-222-1222) right away.

Directions

- when practical, cleanse the affected area by patting or blotting with an appropriate cleansing wipe.
- gently dry by patting or blotting with a tissue or a soft cloth before insertion of suppository.
- detach on suppository from the strip
- separate the two tabs of the white plastic wrap
- with thumb and forefinger of each hand, grasp the tabs and peel downward, unwrapping the suppository
- insert one suppository into the rectum

adults and children 12 years and over: insert one suppository rectally up to 4 times daily

children under 12 years: ask a doctor

Other information

store below 30ºC (86ºF) to avoid melting.

Inactive ingredients

corn starch, methylparaben, propylparaben

PACKAGE LABEL

The product package shown above represents a sample of that currently in use. Additional packaging may also be available.

Major Hemorrhoidal Suppositories 12ct

Distributed by

Major Pharmaceuticals

17177 N. Laurel Park Drive

Suite 233

Livonia, MI 48152

MajorHemSupp.jpg